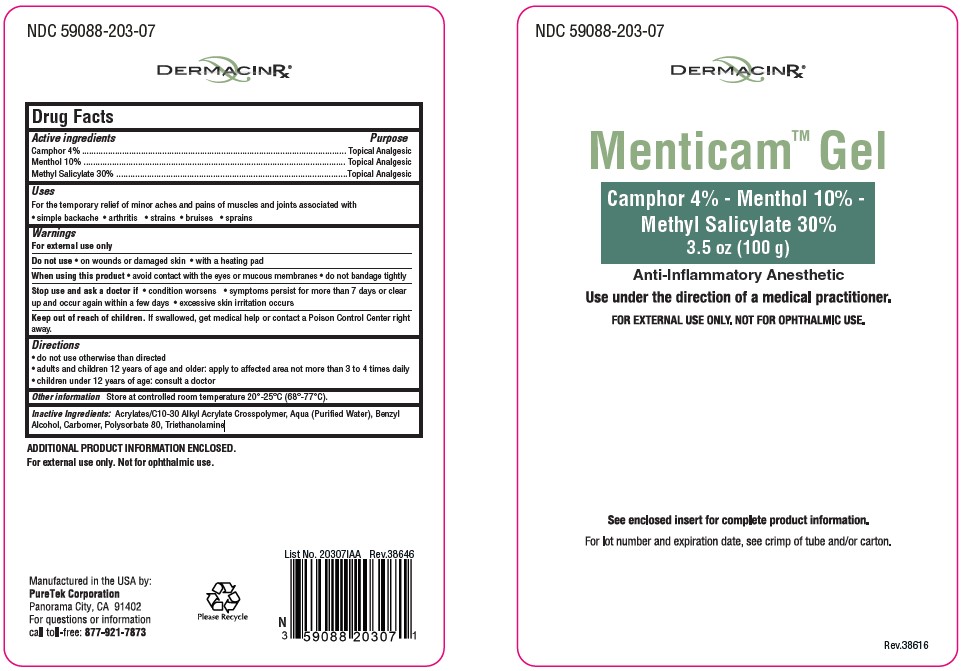 DRUG LABEL: Menticam
NDC: 59088-203 | Form: GEL
Manufacturer: PureTek Corporation
Category: otc | Type: HUMAN OTC DRUG LABEL
Date: 20240405

ACTIVE INGREDIENTS: MENTHOL, UNSPECIFIED FORM 10 g/100 g; METHYL SALICYLATE 30 g/100 g; CAMPHOR (SYNTHETIC) 4 g/100 g
INACTIVE INGREDIENTS: BENZYL ALCOHOL; POLYSORBATE 80; WATER; CARBOMER HOMOPOLYMER, UNSPECIFIED TYPE; ACRYLATES/C10-30 ALKYL ACRYLATE CROSSPOLYMER (60000 MPA.S); TROLAMINE

Menticam Gel

Drug Facts

Active Ingredients

Camphor 4%
Menthol 10%
Methyl salicylate 30%

Purpose

Camphor - Topical analgesic
Menthol - Topical analgesic
Methyl Salicylate - Topical analgesic

Uses

For the temporary relief of minor aches and pains of muscles and joints associated with

- simple bachache
- arthritis
- strains
- bruises
- sprains

Warnings:

For external use only

Do not use

- on wounds or damaged skin
- with a heating pad
- on a child under 12 years of age with arthritis-like conditions

Ask a doctor before use if you have redness over affected area

When using this product

- use only as directed
- avoid contact with the eyes or mucous membranes
- do not bandage tightly

Stop use and ask a doctor if

- condition worsens
- symptoms persist for more than 7 days or clear up and occur again within a few days
- excessive skin irritation occurs

Keep out of reach of children.

If swallowed, get medical help or contact a Poison Control Center right away.

Directions

- do not use otherwise than directed
- adults and children 12 years of age and older: apply to affected area not more than 3 to 4 times daily
- children under 12 years of age: consult a doctor

Other information

Store at controlled room temperature 20°-25°C (68°-77°C).

Avoid excessive heat. Do not use if package is damaged. Keep out of reach of children.

Inactive Ingredients

Acrylates/C10-30 Alkyl Acrylate Crosspolymer, Aqua (Purified Water), Benzyl Alcohol, Carbomer, Polysorbate 80, Triethanolamine

How Supplied

Menticam™ Gel is an anti-inflammatory anesthetic in a 3.5 oz/ 100 g tube.
NDC 59088-203-07